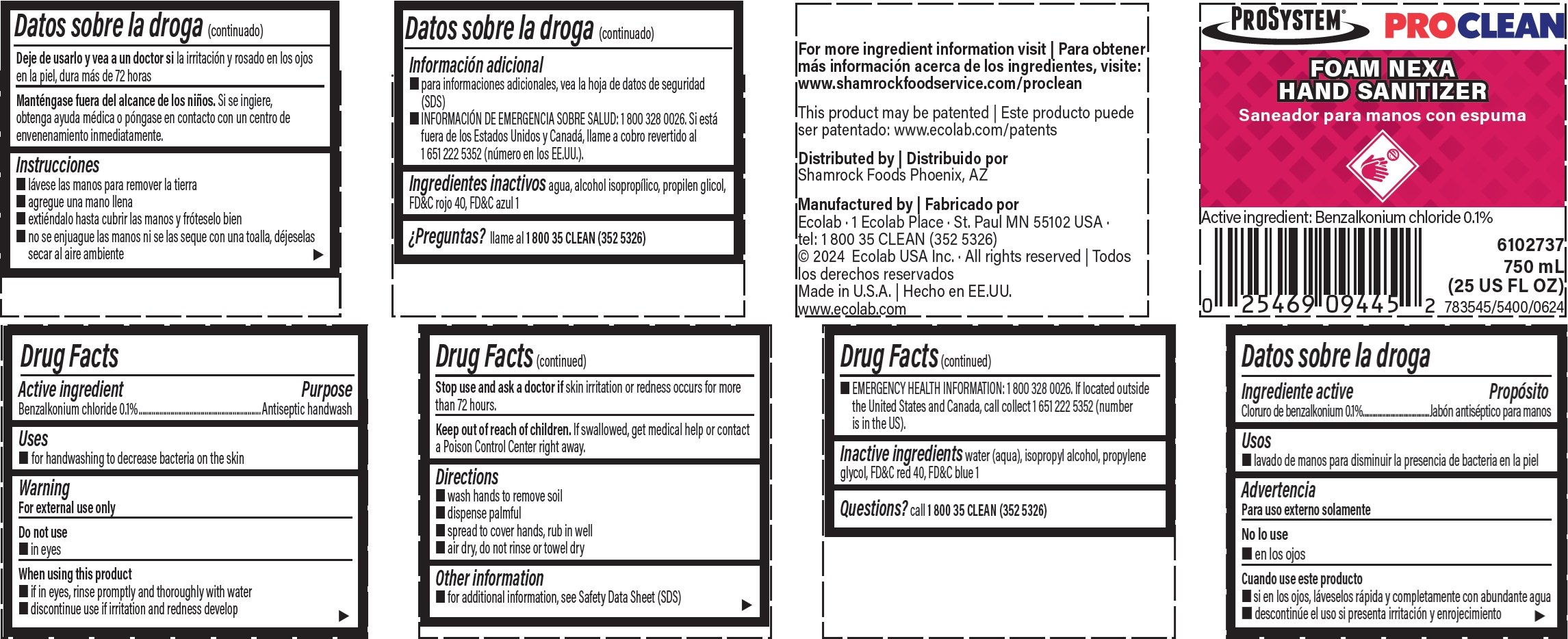 DRUG LABEL: ProClean Foam Nexa Hand Sanitizer
NDC: 47593-657 | Form: SOLUTION
Manufacturer: Ecolab Inc.
Category: otc | Type: HUMAN OTC DRUG LABEL
Date: 20240426

ACTIVE INGREDIENTS: BENZALKONIUM CHLORIDE 0.1 mg/100 mL
INACTIVE INGREDIENTS: WATER; ISOPROPYL ALCOHOL; PROPYLENE GLYCOL; FD&C RED NO. 40; FD&C BLUE NO. 1

Drug Facts

Active ingredient

Benzalkonium chloride 0.1%

Purpose

Antiseptic handwash

Uses

- for handwashing to decrease bacteria on the skin

Warnings

For external use only

Do not use

- in eyes

WHEN USING

- if in eyes, rinse promptly and thoroughly with water
- discontinue use if irritation and redness develop

Stop use and ask a doctor if

- skin irritation or redness occurs for more than 72 hours

KEEP OUT OF REACH OF CHILDREN

Keep our of reach of children. If swallowed, get medical help or contact a Poison Control Center right away.

Direction

- wash hands to remove soil
- dispense palmful
- spread to cover hands, rub in well
- air dry, do not rinse or towel dry

Other information

- for additional information, see Safety Data Sheet (SDS)
- EMERGENCY HEALTH INFORMATION: 1 800 328 0026. If located outside the United States and Canada, call collect 1 651 222 5352 (number is in the US).

INACTIVE INGREDIENT

Inactive ingredients water (aqua), isopropyl alcohol, propylene glycol, FD&C red 40, FD&C blue 1

Questions? call 1 800 35 CLEAN (352 5326)

Principal display panel and representative label

ProSystem

Proclean

Foam Nexa Hand Sanitizer

Active Ingredient: Benzalkonium chloride 0.1%

6102737

750 mL

(25 US FL OZ)

Manufactured by

Ecolab · 1 Ecolab Place · St. Paul MN 55102 USA · tel: 1 800 35 CLEAN (352 5326)

© 2024 Ecolab USA Inc. · All rights reserved

Made in U.S.A.

www.ecolab.com